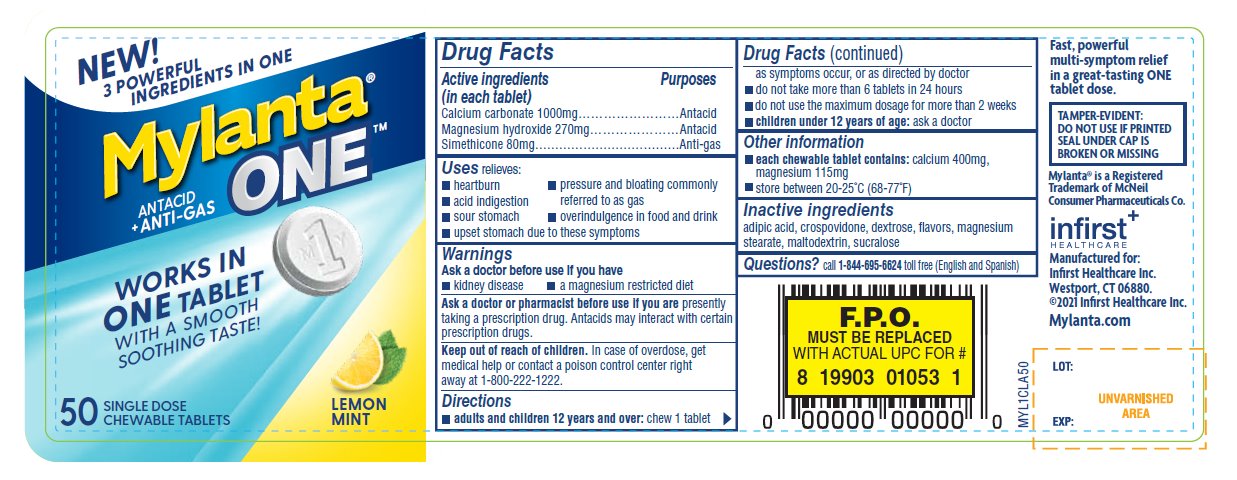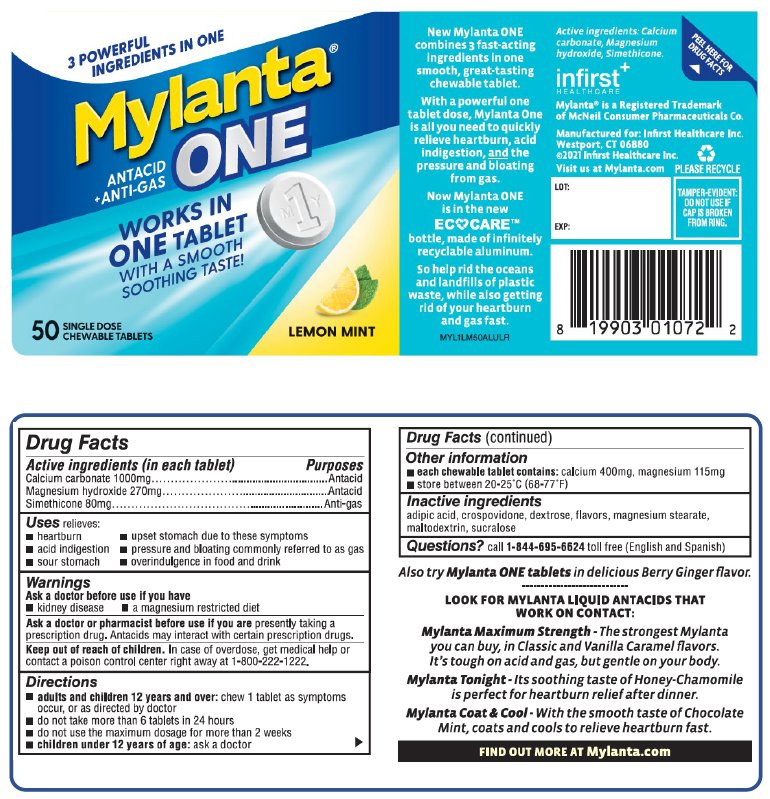 DRUG LABEL: Mylanta One Antacid/Anti-Gas
NDC: 62372-551 | Form: TABLET, CHEWABLE
Manufacturer: Infirst Healthcare Inc.
Category: otc | Type: HUMAN OTC DRUG LABEL
Date: 20231211

ACTIVE INGREDIENTS: CALCIUM CARBONATE 1000 mg/1 1; MAGNESIUM HYDROXIDE 270 mg/1 1; DIMETHICONE 80 mg/1 1
INACTIVE INGREDIENTS: ADIPIC ACID; CROSPOVIDONE; DEXTROSE, UNSPECIFIED FORM; MAGNESIUM STEARATE; MALTODEXTRIN; SUCRALOSE

Drug Facts

Active ingredients (in each tablet)

Calcium carbonate 1000mg

Magnesium hydroxide 270mg

Simethicone 80mg

Purposes

Antacid

Antacid

Anti-gas

Uses

relieves:

- heartburn
- acid indigestion
- sour stomach
- upset stomach due to these symptoms
- pressure and bloating commonly referred to as gas
- overindulgence in food and drink

Warnings

Ask a doctor before use if you have

- kidney disease
- a magnesium restricted diet

Ask a doctor or pharmacist before use if you arepresently taking a prescription drug. Antacids may interact with certain prescription drugs.

Keep out of reach of children

In case of overdose, get medical help or contact a poison control center right away at 1-800-222-1222.

Directions

- adults and children 12 years and over:chew 1 tablet as symptoms occur, or as directed by doctor
- do not take more than 6 tablets in 24 hours
- do not use the maximum dosage for more than 2 weeks
- children under 12 years of age:ask a doctor

Other information

- each chewable tablet contains:calcium 400mg, magnesium 115mg
- store between 20-25°C (68-77°F)

Inactive ingredients

adipic acid, crospovidone, dextrose, flavors, magnesium stearate, maltodextrin, sucralose

Questions?

call 1-844-695-6624toll free (English and Spanish)

Fast, powerful multi-symptom relief in a great-tasting ONE tablet dose.

TAMPER-EVIDENT: DO NOT USE IF PRINTED SEAL UNDER CAP IS BROKEN OR MISSING

Mylanta®is a Registered Trademark of McNeil Consumer Pharmaceuticals Co.

Infirst Healthcare

Manufactured for:
Infirst Healthcare Inc.
Westport, CT 06880.
©2021 Infirst Healthcare Inc.
Mylanta.com

Package/Label Principal Display Panel

NEW!

3 POWERFUL INGREDIENTS IN ONE

Mylanta®
ONETM

ANTACID + ANTI-GAS

WORKS IN ONE TABLET

WITH A SMOOTH SOOTHING TASTE!

50 SINGLE DOSE CHEWABLE TABLETS

LEMON
MINT

Package/Label Principal Display Panel

3 POWERFUL INGREDIENTS IN ONE

Mylanta®
ONE

ANTACID + ANTI-GAS

WORKS IN ONE TABLET

WITH A SMOOTH SOOTHING TASTE!

50 SINGLE DOSE CHEWABLE TABLETS

LEMON
MINT